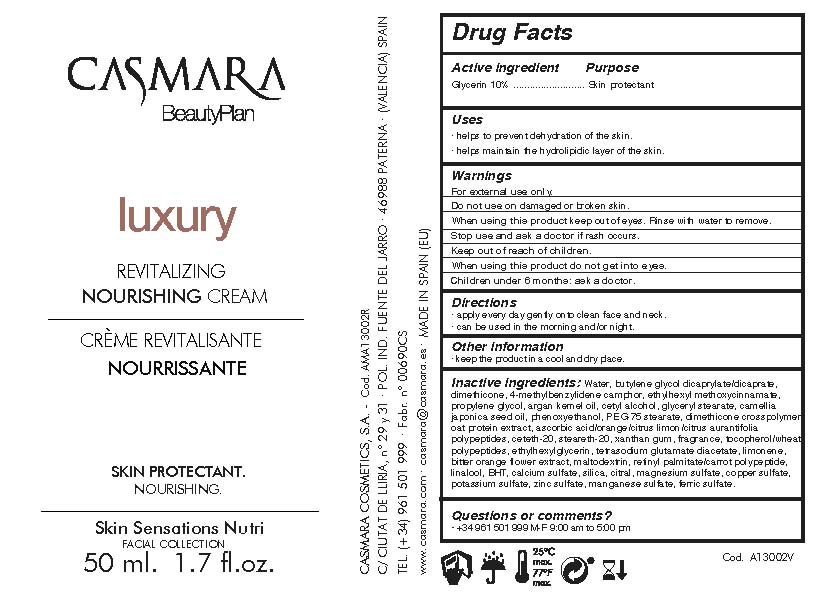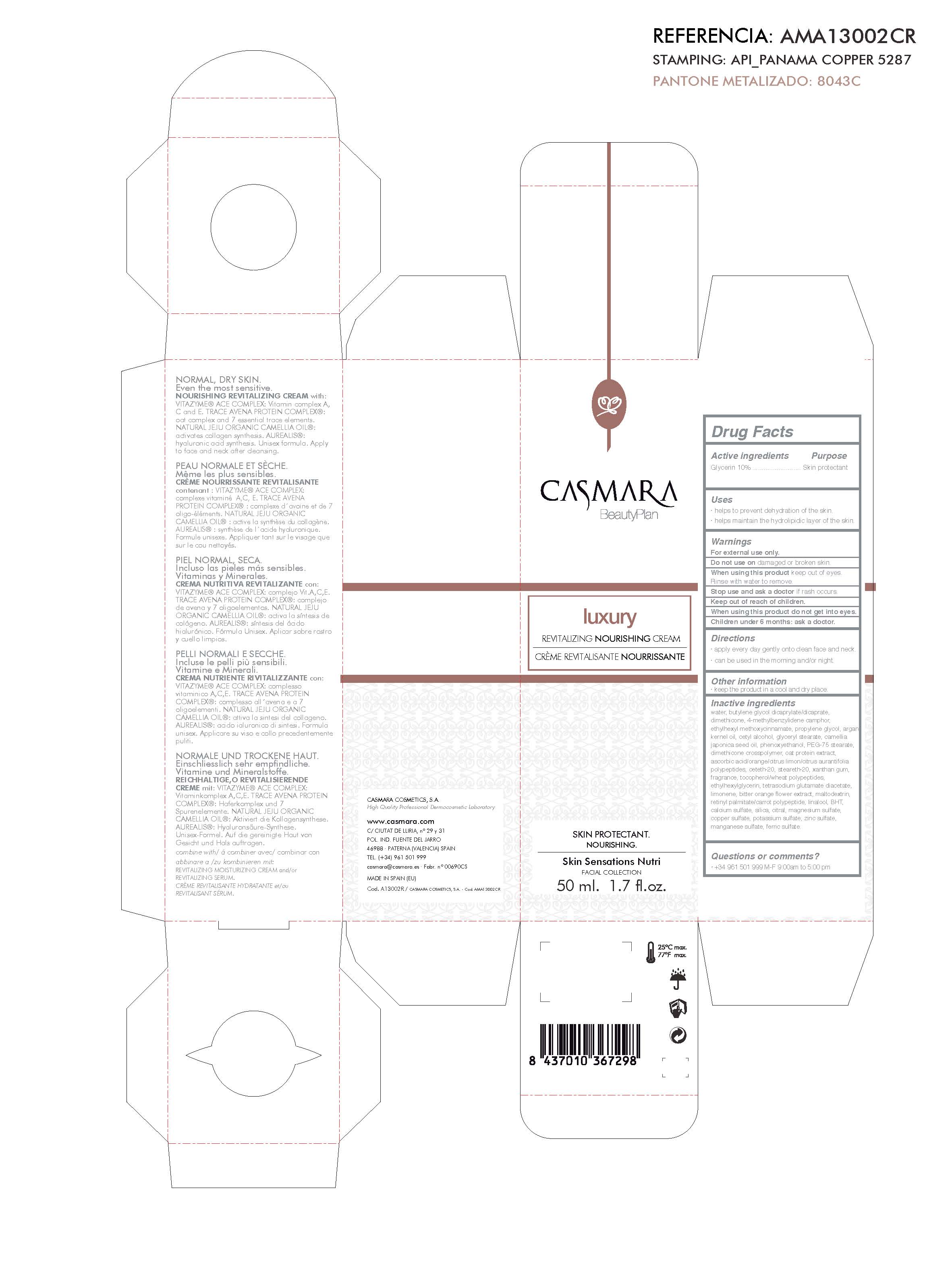 DRUG LABEL: Luxury Revitalizing Nourishing Cream
NDC: 20151-082 | Form: CREAM
Manufacturer: Casmara Cosmetics, SA
Category: otc | Type: HUMAN OTC DRUG LABEL
Date: 20170221

ACTIVE INGREDIENTS: DIMETHICONE 3.36 mg/1 mL; GLYCERIN 10 mg/1 mL
INACTIVE INGREDIENTS: POTASSIUM SULFATE 0.00025 mL/1 mL; FERRIC SULFATE 0.00005 mL/1 mL; MANGANESE SULFATE 0.0001 mL/1 mL; ZINC SULFATE 0.000017 mg/1 mL; CALCIUM SULFATE 0.003 mL/1 mL; LIMONENE, (+)- 0.069 mL/1 mL; MAGNESIUM SULFATE 0.00065 mL/1 mL; CITRAL 0.001 mL/1 mL; HYDRATED SILICA 0.001 mL/1 mL; CETETH-20 0.26 mL/1 mL; ENZACAMENE 3 mL/1 mL; DIPROPYLENE GLYCOL 2.5 mL/1 mL; BASIC COPPER SULFATE 0.0005 mL/1 mL; GLYCERYL STEARATE SE 1.4 mL/1 mL; ETHYLHEXYLGLYCERIN 0.1 mL/1 mL; WATER 59.74 mL/1 mL; XANTHAN GUM 0.2 mL/1 mL; PHENOXYETHANOL 0.9 mL/1 mL; TETRASODIUM GLUTAMATE DIACETATE 0.094 mL/1 mL; CETYL ALCOHOL 1.4 mL/1 mL; HYDROLYZED WHEAT PROTEIN (ENZYMATIC, 3000 MW) 0.5 mL/1 mL; TOCOPHEROL 0.134 mL/1 mL; ARGAN OIL 2 mL/1 mL; BUTYLATED HYDROXYTOLUENE 0.013 mL/1 mL; MALTODEXTRIN 0.036 mL/1 mL; BITTER ORANGE OIL 0.063 mL/1 mL; PERFLUNAFENE 0.2 mL/1 mL; STEARETH-20 0.26 mL/1 mL; ASCORBIC ACID 0.335 mL/1 mL; DIMETHICONE/VINYL DIMETHICONE CROSSPOLYMER (SOFT PARTICLE) 0.64 mL/1 mL; PEG-75 STEARATE 0.68 mL/1 mL; CAMELLIA JAPONICA SEED OIL 1 mL/1 mL; BUTYLENE GLYCOL DICAPRATE 8 mL/1 mL; LINALOOL, (+)- 0.013 mL/1 mL; VITAMIN A PALMITATE 0.031 mL/1 mL; OCTINOXATE 2.99 mL/1 mL

Luxury Revitalizing Nourishing Cream

Warnings

For external use only.

Do not use on damaged or broken skin.

When using this product keep our of the eyes. Rinse with water to remove.

Stop use and ask a doctor if rash occurs.

Keep out of reach of children.

Whhen using this product do not get into eyes.

Children under 6 months: as a doctor.

WARNINGS

Stop use and ask a doctor if rash occurs

Children under 6 months: ask a doctor

Warnings

Keep out of reach of children

Questions or comments?

+ 34 961 501 999 M-F 9:00 am to 5:00 pm

Other Information

. keep the product in a cool and dry place

Directions

. apply every day gently onto clean face and neck

. can be used in the morning and/or night

DOSAGE AND ADMINISTRATION

. apply every day gently onto clean dace and neck

. can be used in the morning and/or night

Uses

. helps to prevent dehydration of the skin.

. helps maintain the hydrolipidic layer of the skin

. helps to combat the signs of ageing

Inactive Ingredients

Water, Butylene Glycol Dicaprylate/Dicaprate, Dimethicone, 4-Methylbenzylidene Camphor , Ethylhexyl methoxycinnamate, Propylene glycol, Argan kernel oil, Cetyl alcohol , Glyceryl stearate, Camellia japonica seed oil, Phenoxyethanol, PEG-75 stearate, Dimethicone crosspolymer, Oat protein extract, Ascorbic acid/Orange/Citrus limon/Citrus aurantifolia polypeptides, Ceteth-20, Steareth-20, Xanthan gum, Fragrance, Tocopherol/Wheat polypeptides, Ethylhexylglycerin, Tetrasodium glutamate diacetate, Limonene, Bitter orangeflower extract, Maltodextrin, Retinyl palmitate/Carrot polypeptide, Linalool, BHT, Calcium sulfate, Silica, Citral, Magnesium sulfate,Copper sulfate, Potassium sulfate, Zinc sulfate, Manganese sulfate, Ferric sulfate

Uses

. helps to prevent dehydration of the skin

. helps maintain the hydrolipidic layer of the skin

. helps to nourish the skin

ACTIVE INGREDIENTS PURPOSE

Glycerin 10%.................... Skin Protectant

Hydra lifting Firming Nourishing Cream See below image

Hydra lifting

Firming Nourishing Cream

Skin Protectant

Nourished Skin